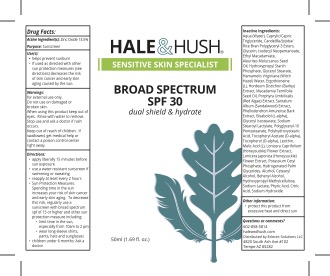 DRUG LABEL: Hale and Hush Broad Spectrum SPF 30
NDC: 83677-610 | Form: CREAM
Manufacturer: Eclectic Solutions LLC
Category: otc | Type: HUMAN OTC DRUG LABEL
Date: 20260112

ACTIVE INGREDIENTS: ZINC OXIDE 13.5 g/100 g
INACTIVE INGREDIENTS: POLYGLYCERYL-10 STEARATE; PHELLODENDRON AMURENSE BARK; LECITHIN, SOYBEAN; MALIC ACID, L-; PEG-60 GLYCERYL STEARATE; POLYHYDROXYSTEARIC ACID (2300 MW); .ALPHA.-TOCOPHEROL ACETATE, D-; WITCH HAZEL; DOCOSANOL; SODIUM LACTATE; CITRIC ACID MONOHYDRATE; MACADAMIA OIL; CAPRYLIC/CAPRIC/LAURIC TRIGLYCERIDE; ISODECYL NEOPENTANOATE; ALEURITES MOLUCCANA SEED; PORPHYRA UMBILICALIS; GLYCERYL ISOSTEARATE; POTASSIUM CETYL PHOSPHATE; HYPROMELLOSES; ERGOTHIONEINE; SANDALWOOD; GLYCERIN; WATER; BARLEY; ALCOHOL; LONICERA CAPRIFOLIUM FLOWER; CETOSTEARYL ALCOHOL; HYDROGENATED PALM GLYCERIDES; LEVOMENOL; HYDROXYPROPYL CORN STARCH (5% SUBSTITUTION BY WEIGHT); ETHYL MACADAMIATE; SODIUM STEAROYL LACTYLATE; FYTIC ACID; SODIUM HYDROXIDE

Hale and Hush Broad Spectrum SPF 30

ACTIVE INGREDIENT

Zinc Oxide 13.50%

PURPOSE

Sunscreen

INDICATIONS AND USAGE

* Help prevent sunburn * if used as directed with other sun protection measures (see Directions), decreases the risk of skin cancer and early skin aging caused by th

WARNINGS

For external use only.

Do not use on damaged or broken skin.

When using this product keep out of eyes. Rinse with water to remove.

Keep out of reach of children. If swallowed, get medical help or contact a poison control center right away.

Directions

- apply liberally 15 minutes before sun exposure
- use a water resistant sunscreen if swimming or sweating
- reapply at least every 2 hours
- Sun Protection Measures.
- Spending time in the sun increases your risk of skin cancer and early skin aging. To decrease this risk, regularly use a sunscreen with broad spectrum spf of 15 or higher and other sun protection measure including:
- limit time in the sun, especially from 10am to 2 pm
- wear long-sleeve shirts, pants, hats and sunglasses
- children under 6 months: Ask a doctor

INACTIVE INGREDIENT

Inactive Ingredients: Aqua (Water), Caprylic/Capric Triglyceride, Candelilla/Jojoba/Rice Bran Polyglyceryl-3 Esters, Glycerin, Isodecyl Neopentanoate, Ethyl Macadamiate, Aleurites Moluccanus Seed Oil, Hydroxypropyl Starch Phosphate, Glyceryl Stearate, Hamamelis Virginiana (Witch Hazel) Water, Ergothioneine [(L), Hordeum Distichon (Barley) Extract, Macadamia Ternifolia Seed Oil, Porphyra Umbilicalis (Red Algae) Extract, Santalum Album (Sandalwood) Extract, Phellodendron Amurense Bark Extract, Bisabolol (L-alpha), Glyceryl Isostearate, Sodium Stearoyl Lactylate, Polyglycery1-10 Pentastearate, Polyhydroxystearic Acid, Tocopheryl Acetate (D-alpha), Tocopherol (D-alpha), Lecithin, Malic Acid (L), Lonicera Caprifolium (Honeysuckle) Flower Extract, Lonicera Japonica (Honeysuckle) Flower Extract, Potassium Cetyl Phosphate, Hydrogenated Palm Glycerides, Alcohol, Cetearyl Alcohol, Behenyl Alcohol, Hydroxypropyl Methylcellulose, Sodium Lactate, Phytic Acid, Citric Acid, Sodium Hydroxide

OTHER SAFETY INFORMATION

Protect this product from excessive heat and direct sun

QUESTIONS

602-858-5814

haleandhush.com

Distributed by Eclectic Solutions LLC

4820 South Ash Ave #102

Tempe AZ 85282